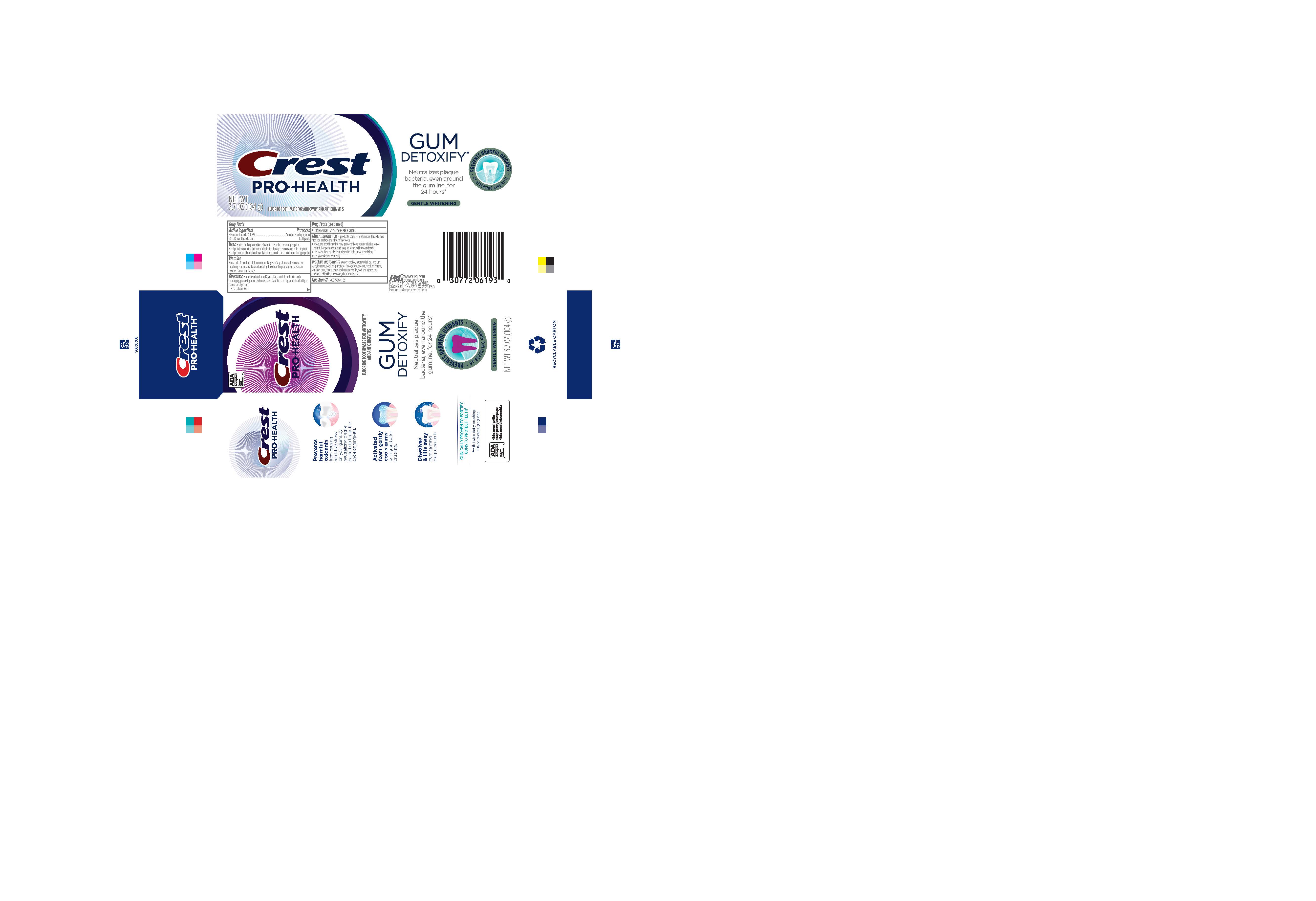 DRUG LABEL: Crest Pro-Health
NDC: 69423-758 | Form: PASTE, DENTIFRICE
Manufacturer: The Procter & Gamble Manufacturing Company
Category: otc | Type: HUMAN OTC DRUG LABEL
Date: 20260108

ACTIVE INGREDIENTS: STANNOUS FLUORIDE 1.5 mg/1 g
INACTIVE INGREDIENTS: SUCRALOSE; STANNOUS CHLORIDE; WATER; HYDRATED SILICA; CARRAGEENAN; SODIUM GLUCONATE; XANTHAN GUM; ZINC CITRATE; SODIUM LAURYL SULFATE; SORBITOL; SODIUM HYDROXIDE; SACCHARIN SODIUM; TITANIUM DIOXIDE; SODIUM CITRATE

Crest Pro-Health Gum Detoxify Gentle Whitening

Drug Facts

Active ingredient

Stannous fluoride 0.454%

(0.15% w/v fluoride ion)

Purposes

Anticavity, antigingivitis toothpaste

Uses

- aids in the prevention of cavities
- helps prevent gingivitis
- helps interfere with the harmful effects of plaque associated with gingivitis
- helps control plaque bacteria that contribute to the development of gingivitis

Warning

Keep out of reach of children under 12 yrs. of age. If more than used for brushing is accidentally swallowed, get medical help or contact a Poison Control Center right away.

Directions

- adults and children 12 yrs. of age and older: Brush teeth thoroughly, preferably after each meal or at least twice a day, or as directed by a dentist or physician.
- do not swallow
- children under 12 yrs. of age: ask a dentist

Other information

- products containing stannous fluoride may produce surface staining of the teeth
- adequate toothbrushing may prevent these stains which are not harmful or permanent and may be

removed by your dentist

- this Crest is specially formulated to help prevent staining
- see your dentist regularly

Inactive ingredients

water, sorbitol, hydrated silica,
sodium lauryl sulfate, sodium gluconate, carrageenan,
flavor, sodium citrate, xanthan gum, zinc citrate, sodium
saccharin, sodium hydroxide, stannous chloride, sucralose,
titanium dioxide

Questions?

1-800-594-4158

DISTR. BY PROCTER & GAMBLE,

CINCINNATI, OH 45202

Principal Display Panel - 104 g tube in carton

ADA

Accepted

American

Dental

Association

CREST

PRO-HEALTH

FLUORIDE TOOTHPASTE FOR

ANTICAVITY AND ANTIGINGIVITIS

GUM DETOXIFY

NEUTRALIZES PLAQUE

BACTERIA, EVEN AROUND THE

GUMLINE, FOR 24 HOURS*

PREVENT HARMFUL OXIDANTS

BY REVERSING GINGIVITIS

GENTLE WHITENING

NET WT 3.7 OZ (104 g)